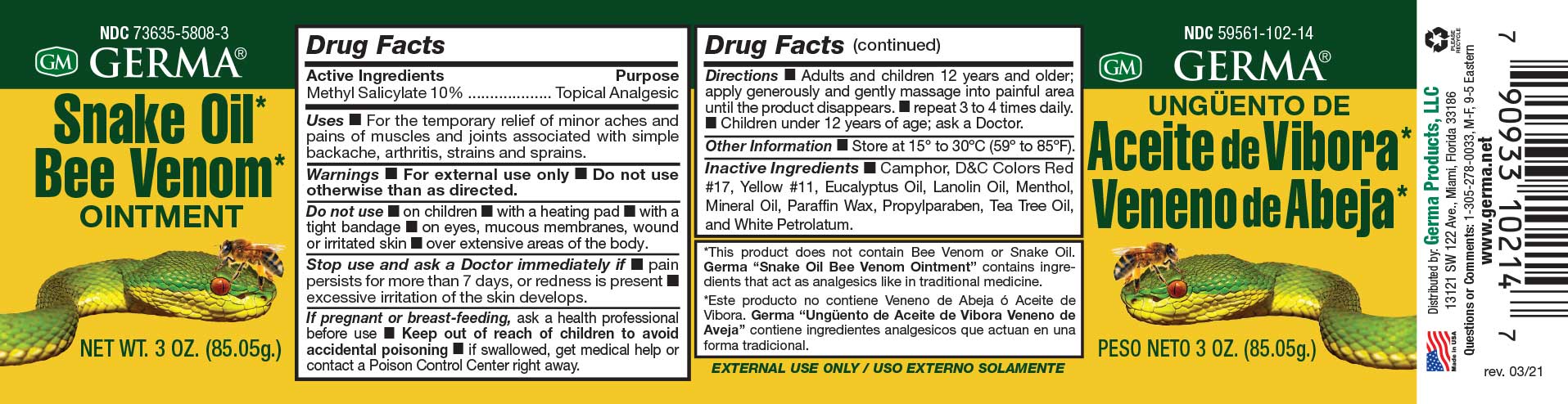 DRUG LABEL: Germa Snake Oil Bee Venom
NDC: 73635-5808 | Form: OINTMENT
Manufacturer: Germa Products, LLC
Category: otc | Type: HUMAN OTC DRUG LABEL
Date: 20251010

ACTIVE INGREDIENTS: METHYL SALICYLATE 100 mg/1 mL
INACTIVE INGREDIENTS: WHITE PETROLATUM; D&C YELLOW NO. 11; D&C RED NO. 17; TEA TREE OIL; MENTHOL; PROPYLPARABEN; LANOLIN OIL; EUCALYPTUS OIL; CAMPHOR (SYNTHETIC); MINERAL OIL; PARAFFIN

Snake Oil Bee Venom Ointment

Active Ingredient

Methyl Salicylate 10%

Uses

For the temporary relief of minor aches and pains of muscles and joints associated with simple backache, arthritis, strains and sprains.

INDICATIONS AND USAGE

For the temporary relief of minor aches and pains of muscles and joints associated with simple backache, arthritis, strains and sprains.

Purpose

Topical Analgesic

Warnings

For external use only. Do not use otherwise than as directed.

Do not use • on children • with a heating pad • with a tight bandage • on eyes, mucous membranes, wound or irritated skin • over extensive areas of the body.

Warnings

Keep out of reach of children to avoid accidental poisoning n if swallowed, get medical help or contact a Poison Control Center right away.

PREGNANCY OR BREAST FEEDING

If pregnant or breast-feeding, ask a health professional before use.

Stop use and ask a Doctor immediately if n pain persists for more than 7 days, or redness is present n excessive irritation of the skin develops.

Other Information

Store at 15º to 30ºC (59º to 85ºF).

Directions

Adults and children 12 years and older; apply generously and gently massage into painful area until the product disappears. n repeat 3 to 4 times daily. n Children under 12 years of age; ask a Doctor.

Inactive Ingredients

Camphor, D&C Colors Red #17, Yellow #11, Eucalyptus Oil, Lanolin Oil, Menthol, Mineral Oil, Paraffin Wax, Propylparaben, Tea Tree Oil, and White Petrolatum.